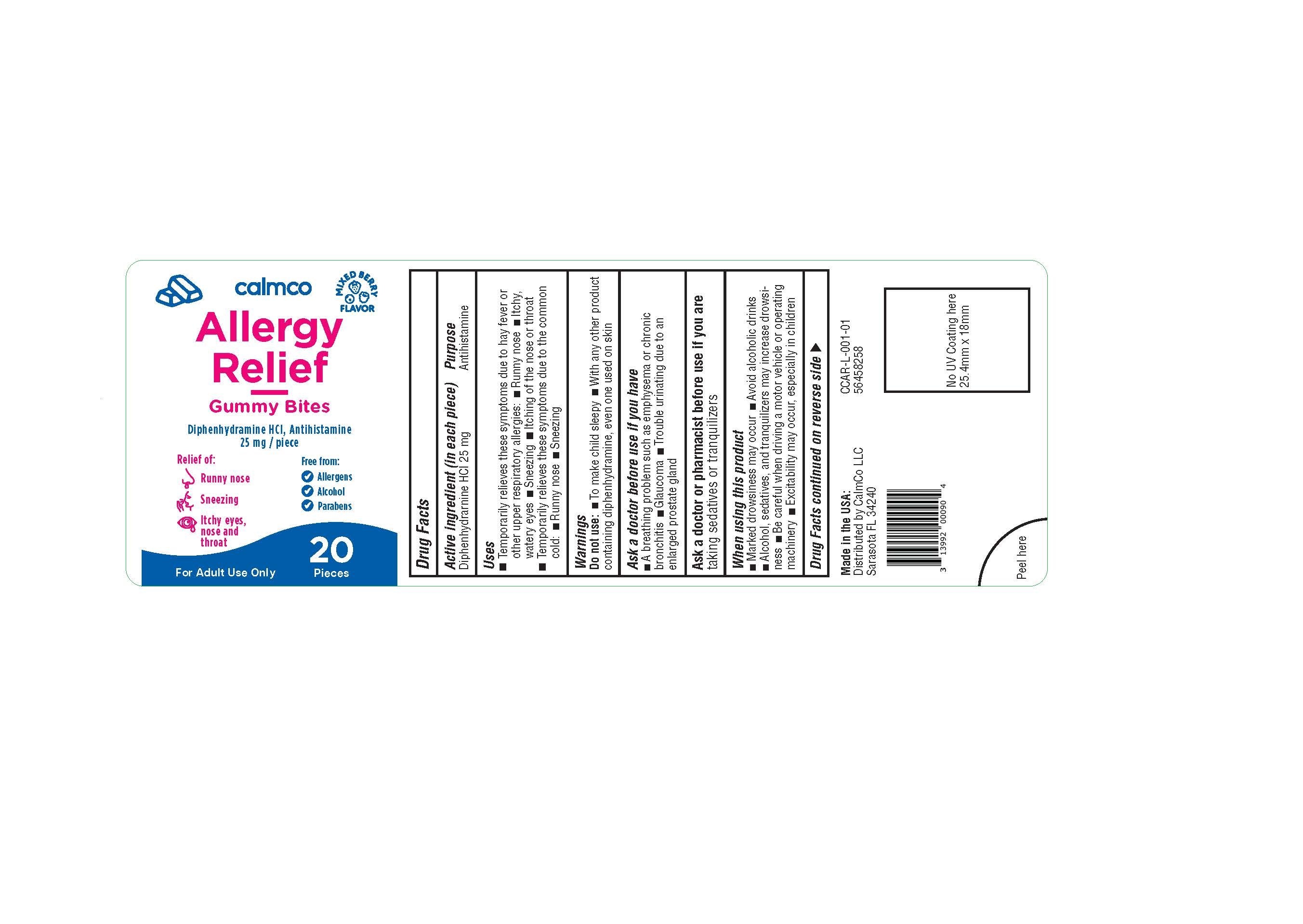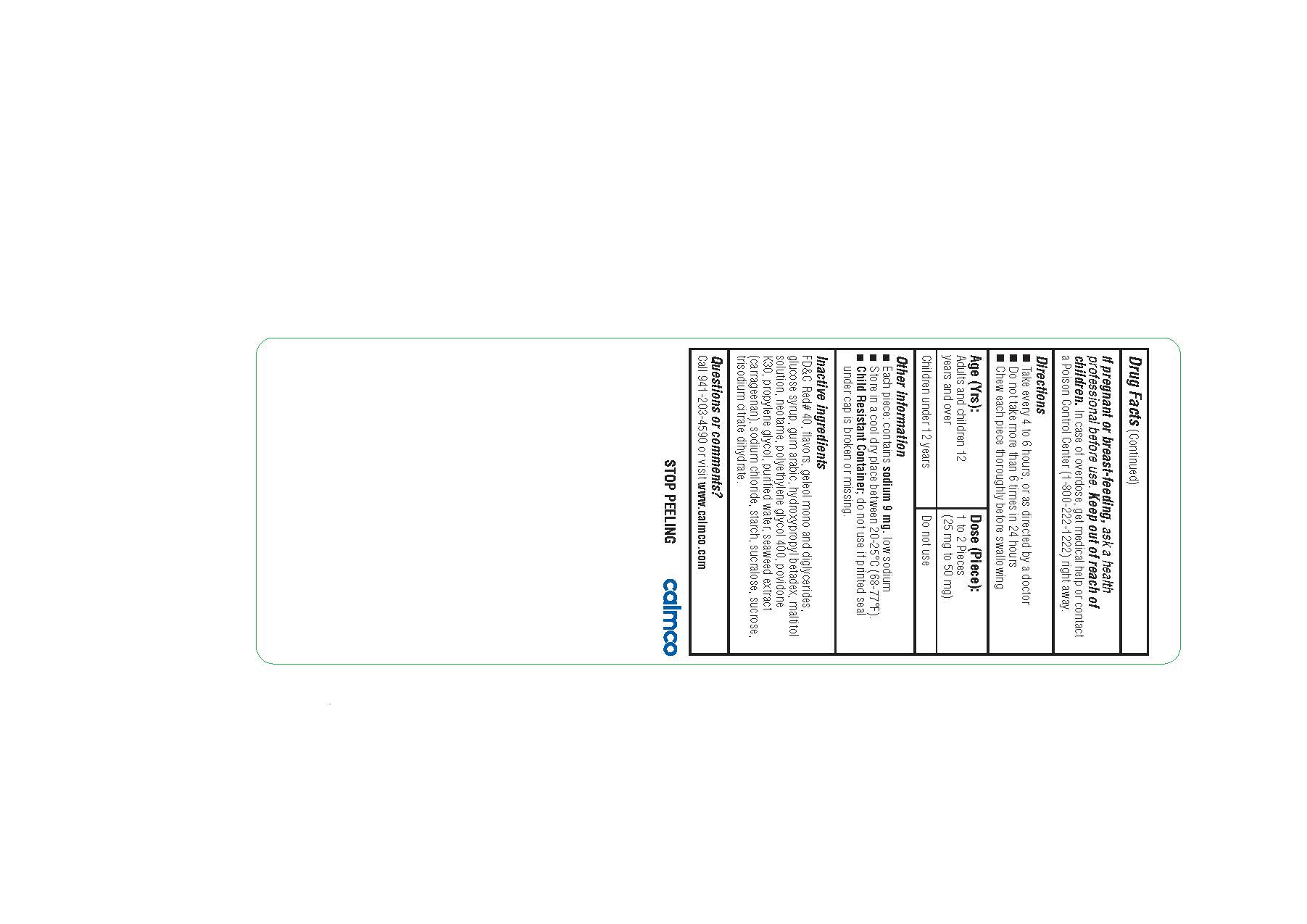 DRUG LABEL: Adult Allergy Relief
NDC: 73282-2520 | Form: BAR, CHEWABLE
Manufacturer: CalmCo
Category: otc | Type: HUMAN OTC DRUG LABEL
Date: 20241207

ACTIVE INGREDIENTS: DIPHENHYDRAMINE HYDROCHLORIDE 25 mg/1 1
INACTIVE INGREDIENTS: PROPYLENE GLYCOL; SUCROSE; CORN SYRUP; NEOTAME; SODIUM CHLORIDE; SUCRALOSE; STARCH, CORN; MALTITOL; GLYCERYL MONO AND DIPALMITOSTEARATE; HYDROXYPROPYL BETADEX; ACACIA; WATER; FD&C RED NO. 40; POLYETHYLENE GLYCOL 400; POVIDONE K30; CARRAGEENAN; TRISODIUM CITRATE DIHYDRATE

Adult Allergy Relief (USP)

Active Ingredient and Purpose

Active ingredient | Purpose
Diphenhydramine HCl 25 mg................. | Anthistamine

Uses

• temporarily relieves these symptoms due to hay fever or other upper respiratory allergies:
■ runny nose
■ itchy, watery eyes
■ sneezing
■ itching of the nose or throat
• temporarily relieves these symptoms due to the common cold:
■ runny nose
■ sneezing

Warnings

Do not use

• To make child sleepy
• with any other product containing diphenhydramine, even one used on skin

ask a doctor before use if you have

• a breathing problem such as emphysema or chronic bronchitis
• glaucoma
• trouble urinating due to an enlarged prostate gland

Ask a doctor or pharmacist before use if you are

taking sedatives or tranquilizers

when using this product

• marked drowsiness may occur
• avoid alcoholic drinks
• alcohol, sedatives, and tranquilizers may increase drowsiness
• be careful when driving a motor vehicle or operating machinery
• excitability may occur, especially in children

If pregnant or breast-feeding

ask a health professional before use.

Keep out of reach of children.

In case of overdose, get medical help or contact a Poison Control Center (1-800-222-1222) right away.

Other Information

• each piece: contains sodium 9 mg.
low sodium
• store in a cool dry place between 20-25°C (68-77°F).
• Child Resistant Container; do not use if printed seal under cap is broken or missing.

Inactive Ingredients

FD&C Red# 40, flavors, geleol mono and diglycerides, glucose syrup, gum atabic,
hydroxypropyl betadex, maltitol solution, neotame, polyethylene glycol 400, povidone K30, propylene
glycol, purified water, seaweed extract (carrageenan), sodium chloride, starch, sucralose, sucrose,
trisodium citrate dihydrate.

Directions

- take every 4 to 6 hours, or as directed by a doctor
- do not take more than 6 times in 24 hours
- chew each piece thoroughly before swallowing

Age (Yrs) | Dose (per piece)
adults and children 12 years and over | 1 to 2 pieces (25mg to 50 mg)
children under 12 years | do not use

Questions or Comments?

Call 941-203-4590 or visit calmco.com